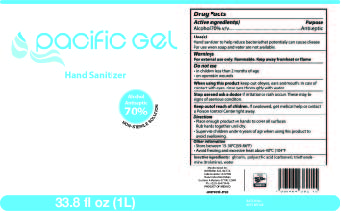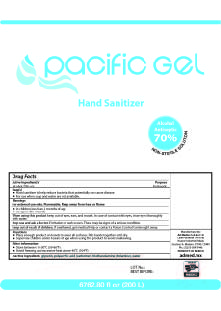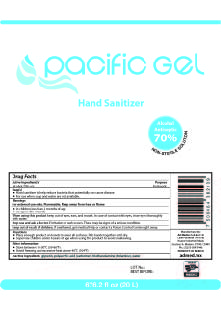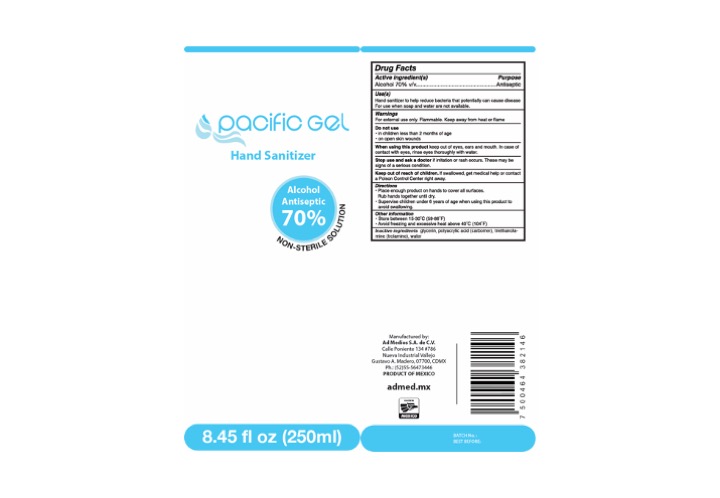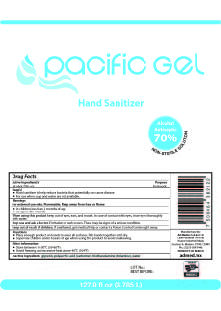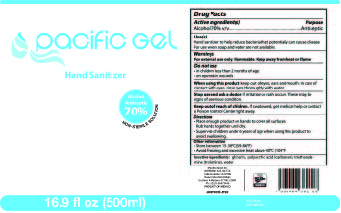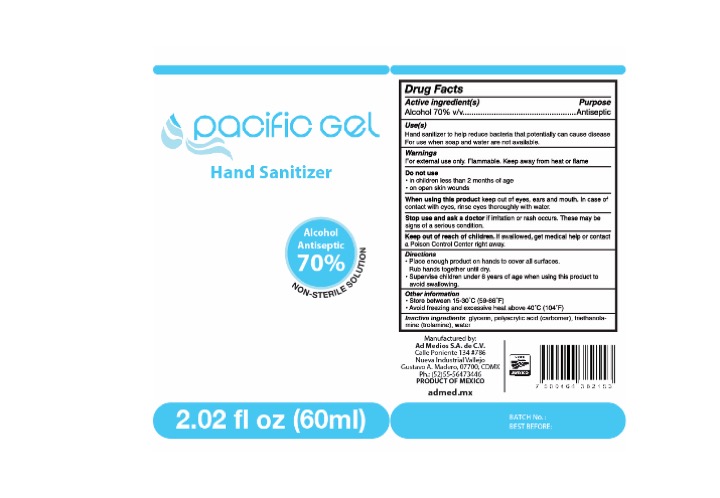 DRUG LABEL: Pacific Gel
NDC: 79058-002 | Form: GEL
Manufacturer: Ad Medios & Mkt, S.A. de C.V.
Category: otc | Type: HUMAN OTC DRUG LABEL
Date: 20200618

ACTIVE INGREDIENTS: ALCOHOL 70 mL/100 mL
INACTIVE INGREDIENTS: TROLAMINE 1 mL/100 mL; POLYACRYLIC ACID (8000 MW) 0.03 mL/100 mL; WATER 28.97 mL/100 mL

Active Ingredient(s)

Alcohol 70% v/v. Purpose: Antiseptic

Purpose

Antiseptic, Hand Sanitizer

Use

Hand Sanitizer to help reduce bacteria that potentially can cause disease. For use when soap and water are not available.

Warnings

For external use only. Flammable. Keep away from heat or flame

Do not use

in children less than 2 months of age
on open skin wounds

When using this product keep out of eyes, ears, and mouth. In case of contact with eyes, rinse eyes thoroughly with water.
Stop use and ask a doctor if irritation or rash occurs. These may be signs of a serious condition.
Keep out of reach of children. If swallowed, get medical help or contact a Poison Control Center right away

Stop use and ask a doctor if irritation or rash occurs. These may be signs of a serious condition.

Keep out of reach of children. If swallowed, get medical help or contact a Poison Control Center right away.

Directions

Place enough product on hands to cover all surfaces. Rub hands together until dry.
Supervise children under 6 years of age when using this product to avoid swallowing.

Other information

Store between 15-30C (59-86F)
Avoid freezing and excessive heat above 40C (104F)

Inactive ingredients

polyacrylic acid (Carbomer), triethanolamine (Trolamine), water

PACKAGE LABEL

60 ML NDC:79058-002-01

PACKAGE LABEL

250 ML NDC:79058-002-02

PACKAGE LABEL

500 ML NDC:79058-002-03

PACKAGE LABEL

1000 ML NDC: 79058-002-04

PACKAGE LABEL

3785 ML NDC: 79058-002-05

PACKAGE LABEL

20L NDC: 79058-002-07

PACKAGE LABEL

200,000 ml NDC: 79058-002-08

PACKAGE LABEL

5000 ml NDC: 79058-002-06